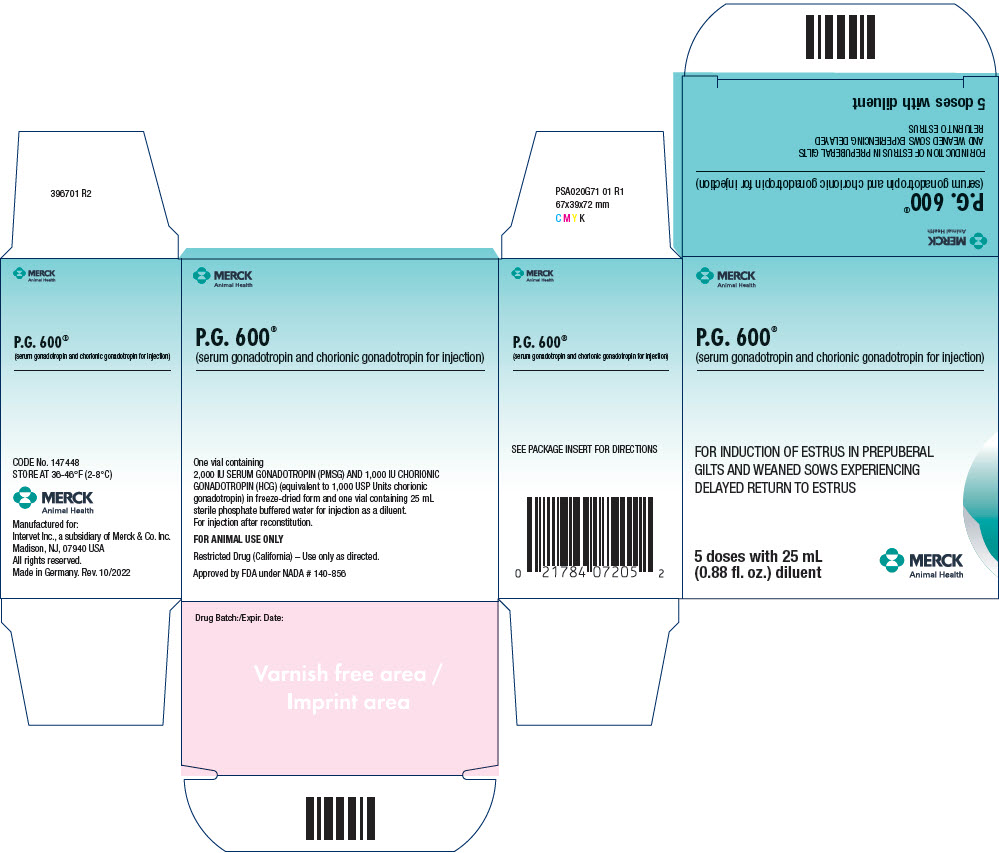 DRUG LABEL: P.G. 600
NDC: 57926-720 | Form: KIT | Route: SUBCUTANEOUS
Manufacturer: Merck Sharp & Dohme Corp.
Category: animal | Type: OTC ANIMAL DRUG LABEL
Date: 20241126

ACTIVE INGREDIENTS: CHORIONIC GONADOTROPIN 1000 [iU]/1 1; SERUM, HORSE 2000 [iU]/1 1
INACTIVE INGREDIENTS: WATER

P.G. 600®

(serum gonadotropin and chorionic gonadotropin for injection)

Approved by FDA under NADA # 140-856

FOR ANIMAL USE ONLY

DESCRIPTION

Gilts normally reach puberty (begin experiencing normal estrous cycles and exhibiting regular estrus or heat) at any time between six and eight months of age, although some gilts will not have exhibited their first estrus at ten months of age. Age at first estrus is influenced by several factors including breed type, season of the year, environmental conditions, and management practice (Hurtgen, 1986).

Sows normally exhibit estrus three to seven days after weaning their litters; however, some otherwise healthy sows may not exhibit estrus for 30 days or more after weaning (Dial and Britt, 1986). The causes of delayed return to estrus in healthy sows are poorly understood, but probably include season of the year (so-called seasonal anestrus; Hurtgen, 1979), adverse environmental conditions, such as high ambient temperatures (Love, 1978), and the number of previous litters, because the condition is more prevalent after the first litter than after later litters (Hurtgen, 1986).

P.G. 600 (serum gonadotropin and chorionic gonadotropin for injection) is a combination of serum gonadotropin (Pregnant Mare Serum Gonadotropin or PMSG) and chorionic gonadotropin (Human Chorionic Gonadotropin or HCG) for use in prepuberal gilts (gilts that have not yet exhibited their first estrus) and in sows at weaning. It is supplied in freeze-dried form with sterile diluent for reconstitution.

In gilts and sows, the action of serum gonadotropin is similar to the action of Follicle-Stimulating Hormone (FSH), which is produced by the animals' anterior pituitary gland. It stimulates the follicles of the ovaries to produce mature ova (eggs), and it promotes the outward signs of estrus (heat).

The action of chorionic gonadotropin in gilts and sows is similar to the action of Luteinizing Hormone (LH), which is also produced by the animals' anterior pituitary gland. It causes the release of mature ova from the follicles of the ovaries (ovulation), and it promotes the formation of corpora lutea, which are necessary for the maintenance of pregnancy once the animals have become pregnant.

The combination of serum gonadotropin and chorionic gonadotropin in P.G. 600 induces fertile estrus in most prepuberal gilts and weaned sows three to seven days after administration (Schilling and Cerne, 1972; Britt et al., 1986; Bates et al., 1991). The animals may then be mated or, in the case of gilts, mating may be delayed until the second estrus after treatment.

NOTE: P.G. 600 IS INTENDED AS A MANAGEMENT TOOL TO IMPROVE REPRODUCTIVE EFFICIENCY IN SWINE PRODUCTION OPERATIONS. TO OBTAIN MAXIMUM BENEFIT FROM THIS PRODUCT, ESTRUS DETECTION AND OTHER ASPECTS OF REPRODUCTIVE MANAGEMENT MUST BE ADEQUATE. IF YOU ARE IN DOUBT ABOUT THE ADEQUACY OF YOUR BREEDING PROGRAM, CONSULT YOUR VETERINARIAN.

HOW SUPPLIED

P.G. 600 is available in:

FIVE DOSE VIALS (order Code No. PG-720-5) - One vial containing white freezedried powder, and one vial containing sterile diluent. When reconstituted, the five dose vial (25 mL) of P.G. 600 contains:

SERUM GONADOTROPIN (PMSG) | 2,000 IU
CHORIONIC GONADOTROPIN (HCG) | 1,000 IU
(equivalent to 1,000 USP Units chorionic gonadotropin)

INDICATIONS AND USAGE

INDICATIONS FOR USE

PREPUBERAL GILTS: P.G. 600 is indicated for induction of fertile estrus (heat) in healthy prepuberal (non-cycling) gilts over five and one-half months of age and weighing at least 85 kg (187 lb.).

SOWS AT WEANING: P.G. 600 is indicated for induction of estrus in healthy weaned sows experiencing delayed return to estrus.

WARNINGS

CAUTIONS

Treatment will not induce estrus in gilts that have already reached puberty (begun to cycle). Gilts that are less than five and one-half months of age or that weigh less than 85 kg (187 lb.) may not be mature enough to continue normal estrus cycles or maintain a normal pregnancy to full term after treatment.

Treatment will not induce estrus in sows that are returning to estrus normally three to seven days after weaning. Delayed return to estrus is most prevalent after the first litter; the effectiveness of P.G. 600 has not been established after later litters. Delayed return to estrus often occurs during periods of adverse environmental conditions, and sows mated under such conditions may farrow smaller than normal litters.

DOSAGE AND ADMINISTRATION

One dose (5 mL) of reconstituted P.G. 600, containing 400 IU serum gonadotropin (PMSG) and 200 IU chorionic gonadotropin (HCG), should be injected subcutaneously into the gilt's or sow's neck behind the ear.

Prepuberal gilts should be injected when they are selected for addition to the breeding herd. Sows should be injected at weaning during periods of delayed return to estrus.

DOSAGE AND ADMINISTRATION

DIRECTIONS FOR USE

FIVE DOSE VIAL: Using a sterile syringe and a sterile 0.90 × 38 mm (20 G × 1½") hypodermic needle, transfer approximately 5 mL of the sterile diluent into the vial of freeze-dried powder. Shake gently to dissolve the powder. Transfer the dissolved product back into the vial of diluent and shake gently to mix. Inject one dose (5 mL) of the reconstituted solution into the gilt's or sow's neck subcutaneously behind the ear.

STORAGE PRECAUTIONS

Store at 36-46°F (2-8°C).

Once reconstituted, P.G. 600 should be used immediately. Unused solution should be disposed of properly and not stored for future use.

Spent hypodermic needles and syringes generated as a result of the use of this product must be disposed of properly in accordance with all applicable Federal, State and local regulations.

REFERENCES

Bates, R.O., B.N. Day, J.H. Britt, L.K. Clark and M.A. Brauer (1991). Reproductive performance of sows treated with a combination of Pregnant Mare's Serum Gonadotropin and Human Chorionic Gonadotropin at weaning in the summer. Journal of Animal Science 69:894.

Britt, J.H., B.N. Day, S.K. Webel and M.A. Brauer (1989). Induction of fertile estrus in prepuberal gilts by treatment with a combination of Pregnant Mare's Serum Gonadotropin and Human Chorionic Gonadotropin. Journal of Animal Science 67:1148.

Dial, G.D., and J.H. Britt (1986). The clinical endocrinology of reproduction in the pig. In: D.A. Morrow (ed.). Current Therapy in Theriogenology 2. W.B. Sanders Company, Philadelphia. p. 905.

Hurtgen, J.P. (1979). Seasonal breeding patterns in female swine. Ph.D. Dissertation, University of Minnesota.

Hurtgen, J.P. (1986). Noninfectious infertility in swine. In: D.A. Morrow (ed.) Current Therapy in Theriogenology 2. W.B. Sanders Company, Philadelphia. p. 962.

Love, R.J. (1978). Definition of a seasonal infertility problem in pigs. Veterinary Record 103:443.

Schilling, E., and F. Cerne (1972). Induction and synchronization of oestrus in prepubertal gilts and anoestrus sows by a PMS/HCG-compound. Veterinary Record 91:471.

220807 R3

Manufactured for:
Intervet Inc., a subsidiary of Merck & Co. Inc.
Madison, NJ, 07940 USA

by:
INTERVET INTERNATIONAL GmbH
UNTERSCHLEISSHEIM, GERMANY
Rev. 07/2024

MERCK
Animal Health

PRINCIPAL DISPLAY PANEL - 25 mL Multi-Dose Vial Carton

MERCK
Animal Health

P.G. 600®
(serum gonadotropin and chorionic gonadotropin for injection)

FOR INDUCTION OF ESTRUS IN PREPUBERAL
GILTS AND WEANED SOWS EXPERIENCING
DELAYED RETURN TO ESTRUS

5 doses with 25 mL
(0.88 fl. oz.) diluent

MERCK
Animal Health